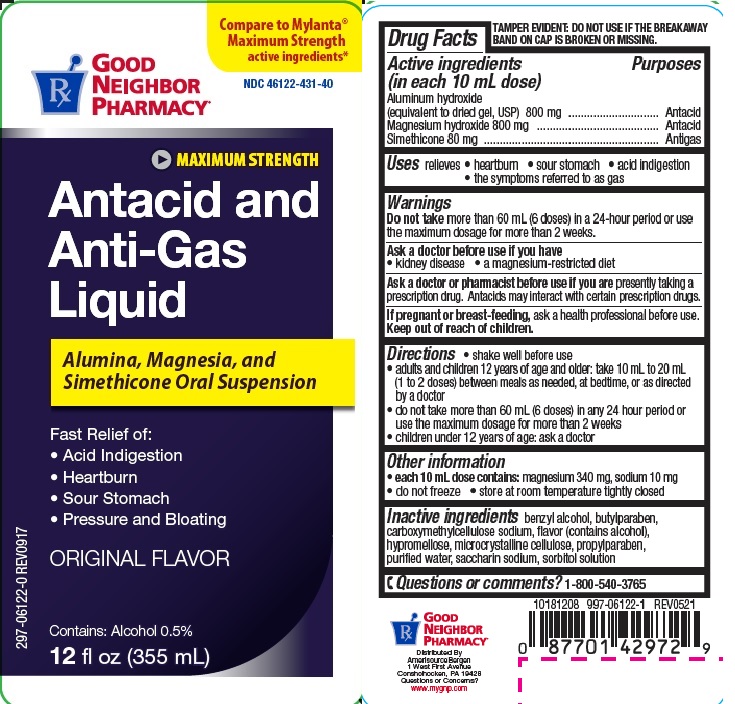 DRUG LABEL: ANTACID ANTIGAS
NDC: 46122-431 | Form: LIQUID
Manufacturer: AMERISOURCEBERGEN DRUG CORPORATION
Category: otc | Type: HUMAN OTC DRUG LABEL
Date: 20231107

ACTIVE INGREDIENTS: ALUMINUM HYDROXIDE 800 mg/10 mL; MAGNESIUM HYDROXIDE 800 mg/10 mL; DIMETHICONE 80 mg/10 mL
INACTIVE INGREDIENTS: BENZYL ALCOHOL; BUTYLPARABEN; CARBOXYMETHYLCELLULOSE SODIUM; HYPROMELLOSES; CELLULOSE, MICROCRYSTALLINE; PROPYLPARABEN; WATER; SACCHARIN SODIUM; SORBITOL SOLUTION

GNP Antacid Anti-Gas max

Active ingredients (in each 10 mL dose)

Aluminum hydroxide (equivalent to dried gel, USP) 800 mg

Magnesium hydroxide 800 mg

Simethicone 80 mg

Purposes

Antacid

Antigas

Uses

relieves

- heartburn
- sour stomach
- acid indigestion
- symptoms of gas

Warnings

Do not take more than 60 mL (6 doses) in a 24-hour period or use
the maximum dosage for more than 2 weeks.

Ask a doctor before use if you have

• kidney disease

• a magnesium-restricted diet

Ask a doctor or pharmacist before use if you are presently taking a prescription drug.

Antacids may interact with certain prescription drugs.

If pregnant or breast-feeding, ask a health professional before use.

Keep out of reach of children.

Directions

- shake well before use
- adults and children 12 years of age and older: take 10 mL to 20 mL (1 to 2 doses) between meals as needed, at bedtime, or as directed by a doctor
- do not take more than 60 mL (6 doses) in any 24 hour period or use the maximum dosage for more than 2 weeks
- children under 12 years of age: ask a doctor

Other information

- each 10 mL dose contains: magnesium 340 mg, sodium 10 mg
- do not freeze
- store at room temperature tightly closed

Inactive ingredients

benzyl alcohol, butylparaben, carboxymethylcellulose sodium, flavor, hypromellose, microcrystalline cellulose, propylparaben, purified water, saccharin sodium, sorbitol solution

Questions or Comments?

1-800-540-3765